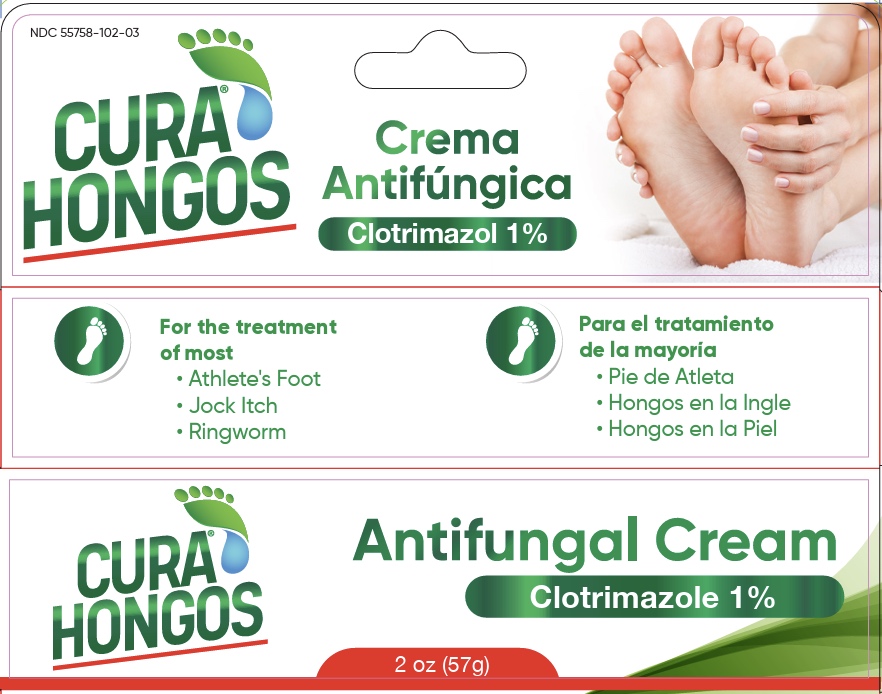 DRUG LABEL: Cura Hongo
NDC: 55758-102 | Form: CREAM
Manufacturer: Pharmadel LLC
Category: otc | Type: HUMAN OTC DRUG LABEL
Date: 20251117

ACTIVE INGREDIENTS: CLOTRIMAZOLE 1 g/100 g
INACTIVE INGREDIENTS: CETETH-20; EDETATE DISODIUM; WATER; SODIUM METABISULFITE; GLYCERYL MONOSTEARATE; MINERAL OIL; CHLOROCRESOL; PROPYLENE GLYCOL; CETOSTEARYL ALCOHOL

Cura Hongo Antifungal (DIL)

Active ingredient & Purpose

.

Active ingredient | Purpose
Clotrimazole 1% w/w | Antifungal

Uses

For the treatment of most:

- athlete's foot
- jock itch
- ring worm

For effective relief of:

- itching
- scaling
- cracking
- burning
- redness
- soreness
- irritation
- discomfort
- chafing associated with jock Itch
- itchy, scaly skin between the toes
- itching, burning feet

Warnings

FOR EXTERNAL USE ONLY.

Do not use

on children under 2 years, unless directed by a doctor.

When using this product

avoid contact with the eyes and mouth

Stop use and ask a doctor if

- irritation occurs
- there is no improvement within 4 weeks (for athlete’s foot and ringworm) or within 2 weeks (for jock itch)

KEEP OUT OF REACH OF CHILDREN.

If swallowed get medical help or contact a Poison Control Center immediately.

Directions

- wash affected area and dry thoroughly
- apply a thin layer of the product over affected area twice daily (morning and night) or as directed by a doctor
- supervise children in the use of this product
- for athlete's foot: pay special attention to spaces between the toes; wear well fitting, ventilated shoes, and change shoes and socks at least once daily.
- for athlete's foot and ringworm: use daily for 4 weeks.
- for jock itch: use daily for 2 weeks.
- if condition persists longer, consult a doctor
- this product is not effective on the scalp or nails

Other information

- store between 59-86˚F (15-30˚C)
- avoid excessive heat and humidity
- do not use if foil seal under cap is punctured, torn, or missing

Inactive ingredients

ceteth-20, cetostearyl alcohol, chlorocresol, edetate disodium, glycerol monostearate, mineral oil, propylene glycol, sodium metabisulfite, water

Questions or comments?

+1-866-359-3478 (M-F) 9AM – 5PM EST or www.pharmadel.com

Dist by/ por:

Pharmadel LLC

New Castle, DE 19720 • www.pharmadel.com

+1-866-359-3478

Made in India / Hecho en India